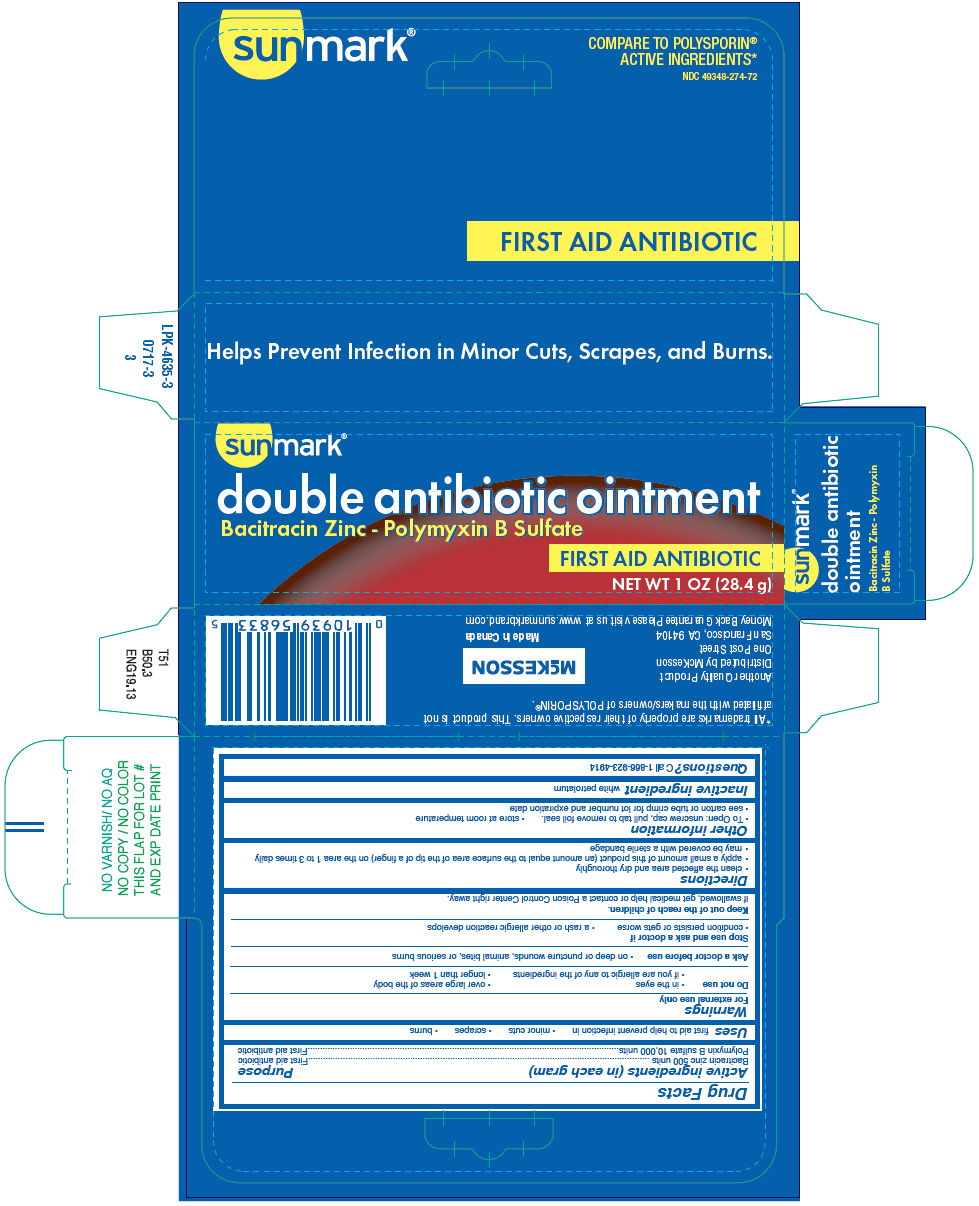 DRUG LABEL: sunmark

NDC: 49348-274 | Form: OINTMENT
Manufacturer: Strategic Sourcing Services LLC
Category: otc | Type: HUMAN OTC DRUG LABEL
Date: 20250714

ACTIVE INGREDIENTS: BACITRACIN ZINC 500 [USP'U]/1 g; POLYMYXIN B SULFATE 10000 [USP'U]/1 g
INACTIVE INGREDIENTS: PETROLATUM

sunmark®
double antibiotic

Drug Facts

ACTIVE INGREDIENT

Active ingredients (in each gram) | Purpose
Bacitracin zinc 500 units | First aid antibiotic
Polymyxin B sulfate 10,000 units | First aid antibiotic

Uses

first aid to help prevent infection in

- minor cuts
- scrapes
- burns

Warnings

For external use only

Do not use

- in the eyes
- over large areas of the body
- if you are allergic to any of the ingredients
- longer than 1 week

Ask a doctor before use

- on deep or puncture wounds, animal bites, or serious burns

Stop use and ask a doctor if

- condition persists or gets worse
- a rash or other allergic reaction develops

Keep out of the reach of children.

If swallowed, get medical help or contact a Poison Control Center right away.

Directions

- clean the affected area and dry thoroughly
- apply a small amount of this product (an amount equal to the surface area of the tip of a finger) on the area 1 to 3 times daily
- may be covered with a sterile bandage

Other information

- To Open: unscrew cap, pull tab to remove foil seal.
- store at room temperature
- see carton or tube crimp for lot number and expiration date

Inactive ingredient

white petrolatum

Questions?

Call 1-866-923-4914

Distributed by McKesson
One Post Street
San Francisco, CA 94104

PRINCIPAL DISPLAY PANEL - 28.4 g Tube Carton

sunmark®

double antibiotic ointment
Bacitracin Zinc - Polymyxin B Sulfate

FIRST AID ANTIBIOTIC

NET WT 1 OZ (28.4 g)